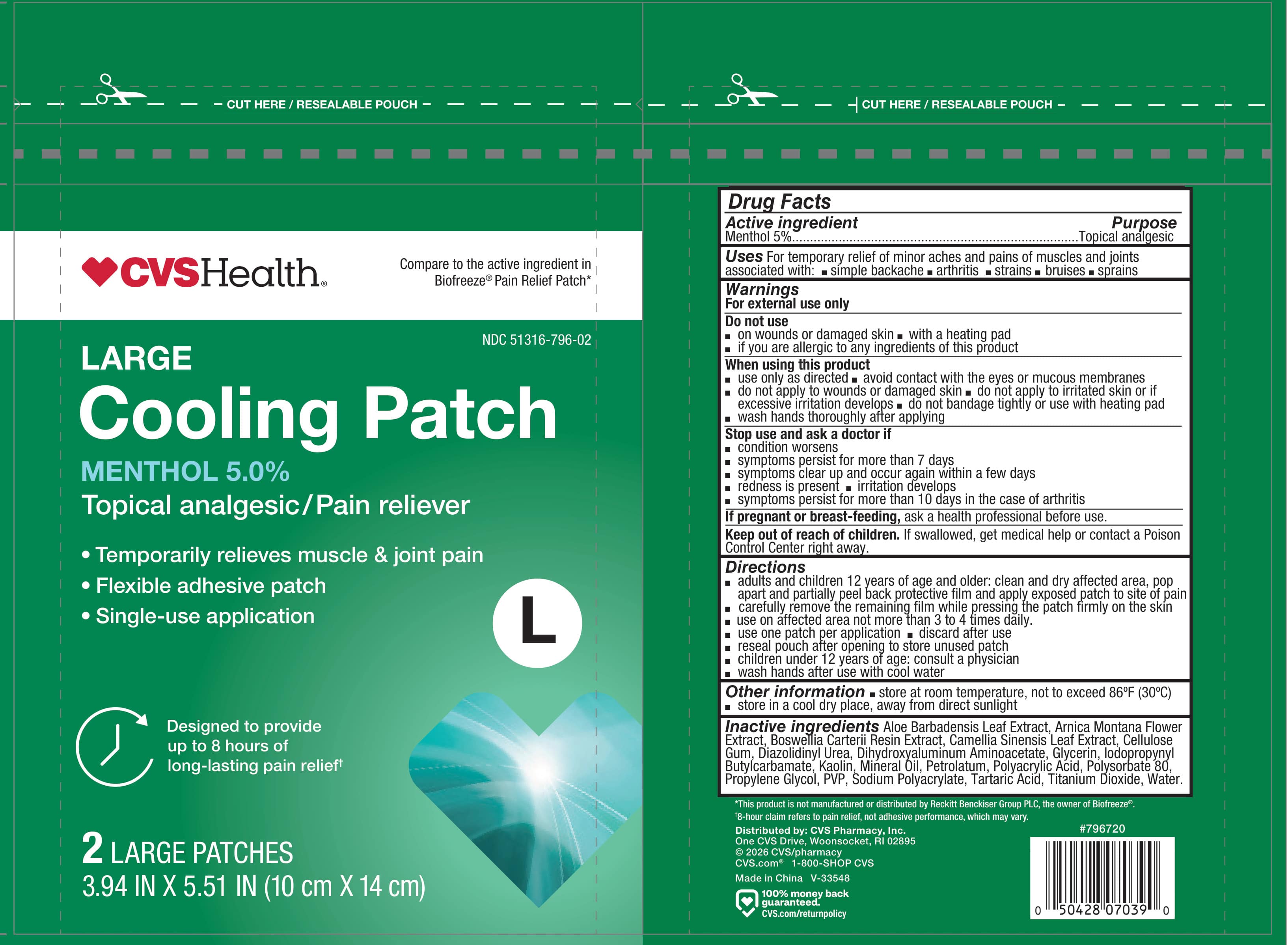 DRUG LABEL: CVS Cooling Patch
NDC: 51316-796 | Form: PATCH
Manufacturer: CVS Pharmacy
Category: otc | Type: HUMAN OTC DRUG LABEL
Date: 20251114

ACTIVE INGREDIENTS: MENTHOL, UNSPECIFIED FORM 0.5 g/10 g
INACTIVE INGREDIENTS: DIHYDROXYALUMINUM AMINOACETATE; TARTARIC ACID; CAMELLIA SINENSIS LEAF; SODIUM POLYACRYLATE (8000 MW); PVP; WATER; ALOE BARBADENSIS LEAF JUICE; TITANIUM DIOXIDE; GLYCERIN; IODOPROPYNYL BUTYLCARBAMATE; ARNICA MONTANA FLOWER WATER; CARBOXYMETHYLCELLULOSE SODIUM; PETROLATUM; KAOLIN; POLYACRYLIC ACID (8000 MW); POLYSORBATE 80; DIAZOLIDINYL UREA; FRANKINCENSE; MINERAL OIL; PROPYLENE GLYCOL

CVS Cooling Patch

Active ingredient

Menthol 5%

Purpose

Topical analgesic

Uses

For temporary relief of minor aches and pains of muscles and joints associated with:

- simple backache
- arthritis
- strains
- bruises
- sprains

Warnings

For external use only

Do not use

- on wounds or damaged skin
- with a heating pad
- if you are allergic to any ingredients of this product

When using this product

- use only as directed
- avoid contact with the eyes and mucous membranes
- do not apply to wounds or damaged skin
- do not apply to irritated skin or if excessive irritationd evelops
- do not bandage tightly or use with heating pad
- wash hands thoroughly after applying

Stop use and ask a doctor if

- condition worsens
- symptoms persist for more than 7 days
- symptoms clear up and occur again within a few days
- redness is present
- irritation develops
- sympotoms persist for more than 10 days in the case of arthritis

If pregnant or breast-feeding

ask a health professional before use.

Keep out of reach of children.

If wallowed, get medical help or contact a Poison Control Center right away.

Directions

- adults and children 12 years of age and older: clean and dry affected area, pop apart and partially peel back protective film and apply exposed patch to site of pain
- carefully remove the remaining film while pressing the patch firmly on the skin
- use on affected area not more than 3 to 4 times daily
- use one patch per application
- discard after use
- reseal pouch after opening to store unused patch
- children under 12 years of age: consult a physician
- wash hands after use with cool water

Other information

- store at room temperature, not to exceed 86°F (30°C)
- store in a cool dry place, away from direct sunlight

Inactive ingredients

Aloe Barbadensis Leaf Extract, Arnica Montana Flower Extract, Boswellia Carterii Resin Extract, Camellia Sinensis Leaf Extract, Cellulose Gum, Diazolidinyl Urea, Dihydroxyaluminum Aminoacetate, Glycerin, Iodopropynyl Butylcarbamate, Kaolin, Mineral Oil, Petrolatum, Polyacrylic Acid, Polysorbate 80, Propylene Glycol, PVP, Sodium Polyacrylate, Tartaric Acid, Titanium Dioxide, Water.

Principal Display Panel - Pouch Label

CVS Health®

Compare to the active ingredient in Biofreeze® Pain Relief Patch*

NDC 51316-796-02

Large

Cooling Patch

Menthol 5.0%

Topical analgesic/Pain reliever

Temporarily relieves muscle & joint pain
Flexible adhesive patch
Single-use application

Designed to provide up to 8 hours of long-lasting pain relief†

2 Large Patches

3.94 in x 5.51 in (10 cm X 14 cm)